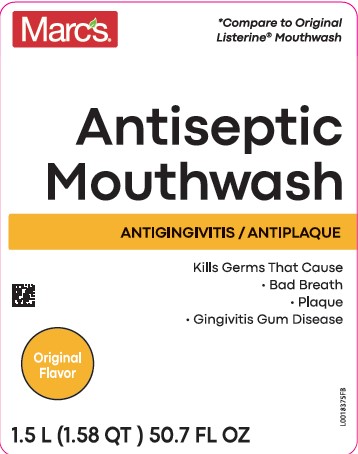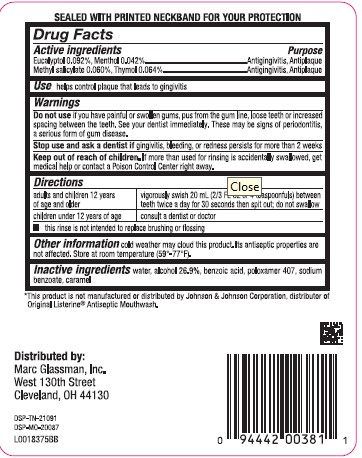 DRUG LABEL: Antiseptic Mouth Rinse
NDC: 68998-318 | Form: MOUTHWASH
Manufacturer: Marc Glassman, Inc
Category: otc | Type: HUMAN OTC DRUG LABEL
Date: 20260204

ACTIVE INGREDIENTS: EUCALYPTOL 0.92 mg/1 mL; MENTHOL 0.42 mg/1 mL; METHYL SALICYLATE 0.6 mg/1 mL; THYMOL 0.64 mg/1 mL
INACTIVE INGREDIENTS: WATER; ALCOHOL; BENZOIC ACID; POLOXAMER 407; SODIUM BENZOATE; CARAMEL

Marc's 318.003/318AH-AI
Antiseptic Mouthrinse

Other Safety Information

SEALED WITH PRINTED NECKBAND FOR YOUR PROTECTION

Active ingredients

Eucalyptol 0.092%

Menthol 0.042%

Methyl salicylate 0.060%

Thymol 0.064%

Purpose

Antigingivitis, Antiplaque

Use

helps control plaque that leads to gingivitis

Warnings

for this product

Do not use

If you have painful or swollen gums, pus from the gum line, loose teeth or increased spacing between the teeth. See your dentist immediately. These may be signs of periodontitis, a serious form of gum disease.

Stop use and ask a dentist if

gingivitis, bleeding, or redness persists for more than 2 weeks

Keep out of reach of chrildren

If more than used for rinsing is accidentally swallowed, get medical help or contact a Poison Control Center right away.

Directions

adults and children 12 years of age and older - vigorously swish 20 mL (2/3 FL OZ or 4 teaspoonfuls) between teeth twice a day for 30 seconds then spit out; do not swallow

children under 12 years of age - consult a dentist or doctor

- This rinse is not intended to replace brushing or flossing

Other information

cold weather may cloud this product. Its antiseptic properties are not affected. Store at room temperature (59°-77°F).

Inactive ingredients

water, alcohol 26.9%, benzoic acid, poloxamer 407, sodium benzoate, caramel

ADVERSE REACTION

*This product is not manufactued or distributed by Johnson & Johnson Corporation, distributor of Original Listerine® Antiseptic Mouthwash.

Distributed by:

Marc Glassman, Inc.

West 130th Street

Cleveland, OH 44130

DSP-TN-21091

DSP-MO-20087

Principal display panel

Marc's

*Compare to Original Listerine® Mouthwash

Antseptic

Mouthwash

Antigingivitis/Antiplaque

Kills Germs that Cause

- Bad Breath
- Plaque
- Gingivitis Gum Disease

Original Flavor

1.5 L (1.58 QY) 50.7 FL OZ